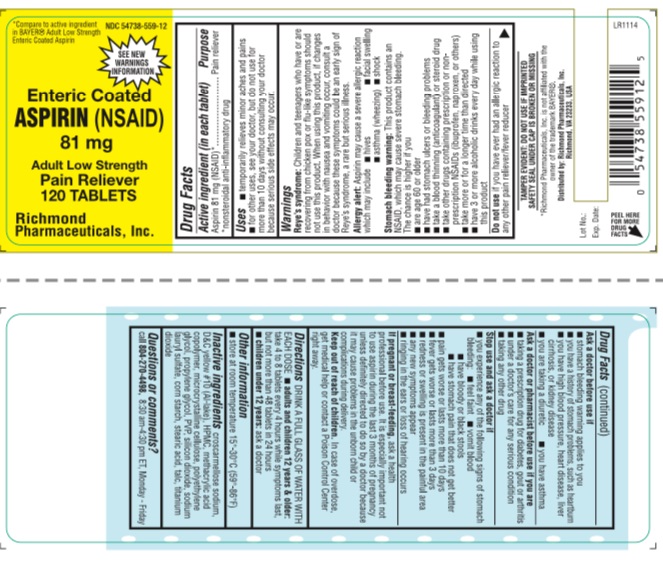 DRUG LABEL: Aspirin
NDC: 54738-559 | Form: TABLET
Manufacturer: Richmond Pharmaceuticals, Inc.
Category: otc | Type: HUMAN OTC DRUG LABEL
Date: 20171101

ACTIVE INGREDIENTS: ASPIRIN 81 mg/1 1
INACTIVE INGREDIENTS: CROSCARMELLOSE SODIUM; D&C YELLOW NO. 10; HYPROMELLOSES; METHACRYLIC ACID; CELLULOSE, MICROCRYSTALLINE; POLYETHYLENE GLYCOL 1000; PROPYLENE GLYCOL; POVIDONE; SILICON DIOXIDE; SODIUM LAURYL SULFATE; STARCH, CORN; STEARIC ACID; TALC; TITANIUM DIOXIDE

ENTERIC COATED ASPIRIN 81mg

Active Ingredient

(in each tablet)

Aspirin 81 mg (NSAID) *

*nonsteroidal anti-inflammatory drug

Purpose

Pain Reliever

Uses

- temporarily relieves minor aches and pains
- for other uses, see your doctor, but do not use for more than 10 days without consulting your doctor because serious side effects may occur.

Warnings

Reye’s Syndrome: Children and teenagers who have or are recovering from chicken pox or flu-like symptoms should not use this product. When using this product, if changes in behavior with nausea and vomiting occur, consult a doctor because these symptoms could be an early signs of Reye’s syndrome, a rare but serious illness.

Allergy Alert: Aspirin may cause a severe allergic reaction which may include

- hives
- asthma (wheezing)
- shock
- facial swelling
  Stomach Bleeding Warning: This product contains an NSAID, which may cause severe stomach bleeding. The chance is higher if you
- are age 60 or older
- have had stomach ulcers or bleeding problems
- take a blood-thinning (anticoagulant) or steroid drug
- takes other drugs containing prescription or nonprescription NSAIDs (ibuprofen, naproxen, others)
- takes more or for a longer time than directed
- have 3 or more alcoholic drinks every day while using this product.
  Do not use
- if you have ever had an allergic reaction to any other pain reliever / fever reducer
  Ask a doctor before use if
- stomach bleeding warning applies to you
- you have a history of stomach problems, such as heartburn
- you have high blood pressure, heart disease, lever cirrhosis, or kidney disease
- you are taking a diuretic
- you have asthma
  Ask a doctor or pharmacist before use if you are
- taking a prescription drug for diabetes, gout or arthritis
- taking any other drug
- under a doctor’s care for any serious condition
  Stop use and ask a doctor if
- you experiences any of the following signs of stomach bleeding:
- feel faint
- vomit blood
- have bloody or black stools
- have stomach pain that does not get better
- pain gets worse or lasts more than 10 days
- fever gets worse or lasts more than 3 days
- redness or swelling is present in the painful area
- any new symptoms appear
- ringing in the ears or a loss of hearing occurs
  If pregnant or breast-feeding, ask a health professional before use. It is especially important not to use aspirin during the last 3 months of pregnancy unless definitely directed to do so by a doctor because it may cause problems in the unborn child or complications during delivery.

Keep out of reach of children.

In case of overdose, get medical help or contact a Poison Control Center right away.

Directions

DRINK A FULL GLASS OF WATER WITH EACH DOSE

- adults and children 12 years and older : take 4 to 8 tablets every 4 hours while symptoms last, but not more than 48 tablets in 24 hours.
- Children under 12 years: ask a doctor

Other Information

- store at 15-30 °C (59-86 °F)

Inactive Ingredients

croscarmellose sodium, D&C Yellow #10 (Al-Lake), HPMC, methacrylic acid copolymer, microcrystalline cellulose, polyethylene glycol, propylene glycol, PVP, silicon dioxide, sodium lauryl sulfate, corn starch, stearic acid, talc, titanium dioxide

Questions or Comments

TAMPER EVIDENT: DO NOT USE IF IMPRINTED SAFETY SEAL UNDER CAP IS BROKEN OR MISSING

Safer for your stomach than pain or Buffered Aspirin

call 804-270-4498, 8.30 am-4.30 pm ET, Monday - Friday

PACKAGE LABEL.PRINCIPAL DISPLAY PANEL

NDC: 54738-559-12– 120 Tablets

NDC: 54738-559-25 - 240 Tablets

NDC: 54738-559-03 - 1000 Tablets